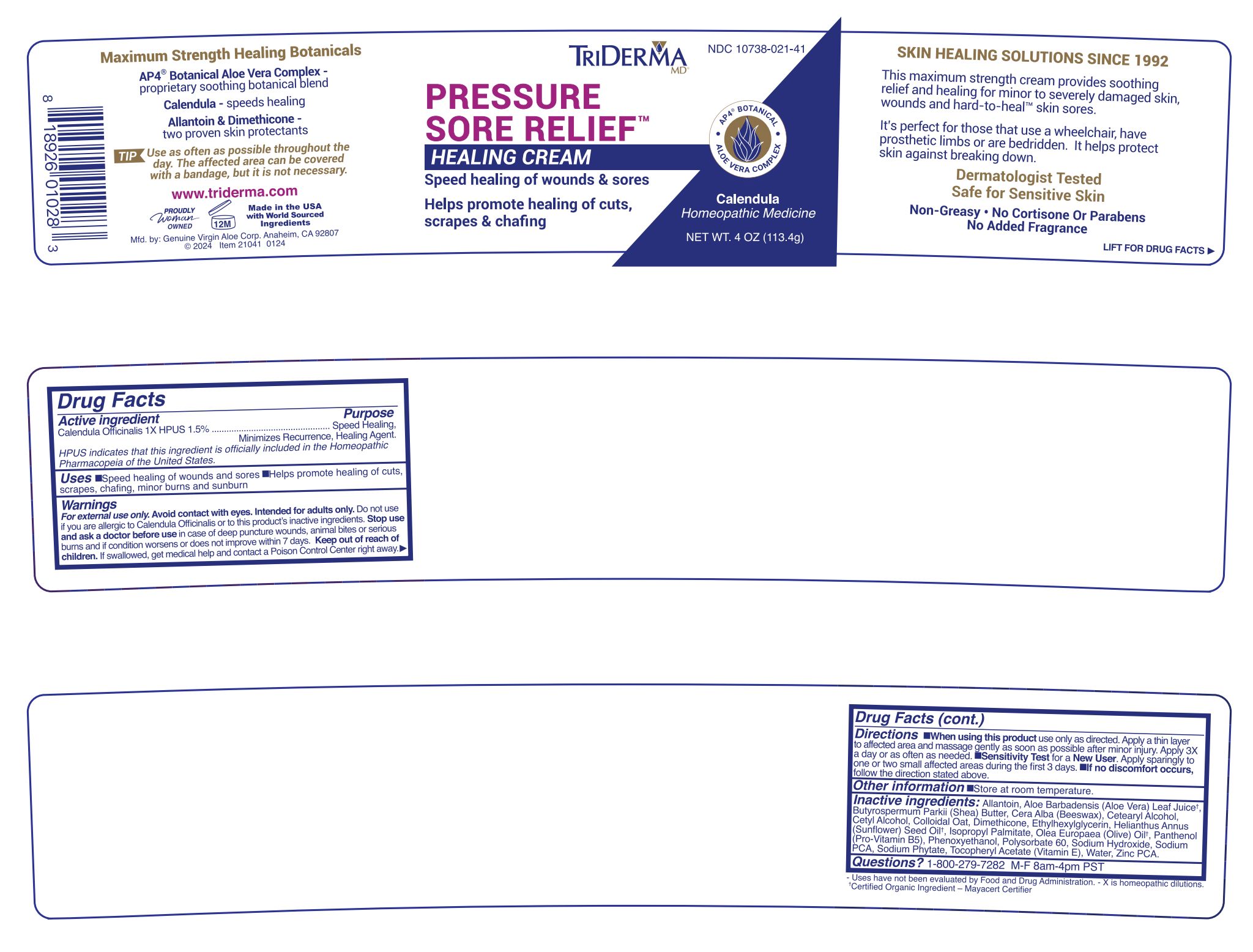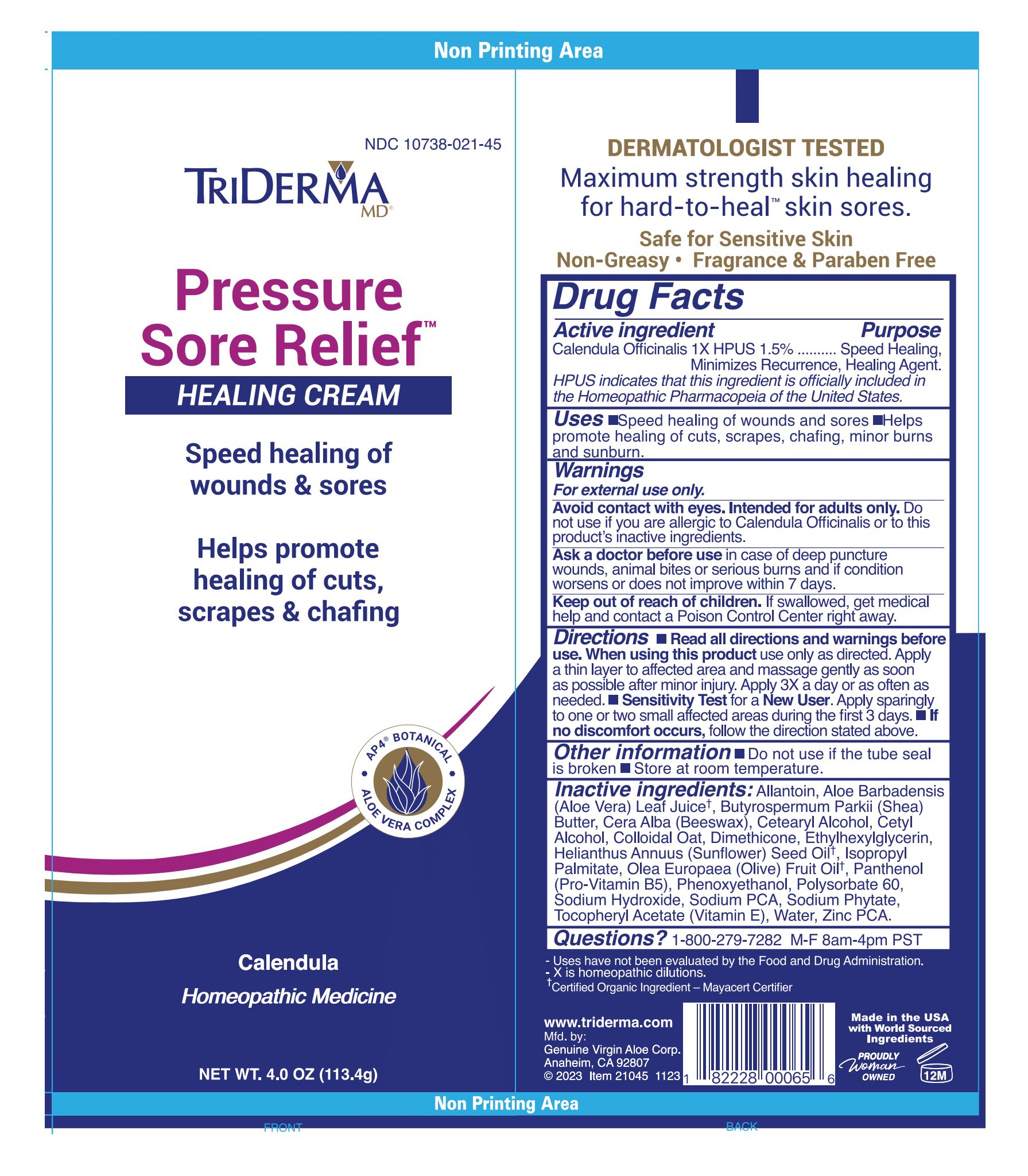 DRUG LABEL: TRIDERMA PRESSURE SORE RELIEF
NDC: 10738-210 | Form: CREAM
Manufacturer: Genuine Virgin Aloe Corporation
Category: homeopathic | Type: HUMAN OTC DRUG LABEL
Date: 20260124

ACTIVE INGREDIENTS: CALENDULA OFFICINALIS FLOWERING TOP 1.5 g/100 g
INACTIVE INGREDIENTS: WATER; CETOSTEARYL ALCOHOL; ISOPROPYL PALMITATE; POLYSORBATE 60; YELLOW WAX; DIMETHICONE; ALLANTOIN; ZINC PIDOLATE; OATMEAL; ALOE VERA LEAF; SHEA BUTTER; .ALPHA.-TOCOPHEROL ACETATE; PANTHENOL; CETYL ALCOHOL; SODIUM PYRROLIDONE CARBOXYLATE; PHYTATE SODIUM; SODIUM HYDROXIDE; PHENOXYETHANOL; ETHYLHEXYLGLYCERIN

TRIDERMA Pressure Sore Relief Healing Cream

Active ingredient

Calendula Officinalis 1X HPUS 1.5%

Purpose

Speed healing, Minimizes recurrence, healing agent.

HPUS indicates that this ingredient is officially included in the Homeopathic Pharmacopeia of the United States.

INDICATIONS AND USAGE

Uses •speed healing of wounds, sores, acne and lip sores •helps promote healing of cuts, scrapes, chafing, minor burns and sunburn

Warnings For external use only.

Avoid contact with eyes. Intended for adults only. Do not use if you are allergic to Calendula Officinalis or to this product's inactive ingredients.

Stop use and ask a doctor before use in case of deep puncture wounds, animal bites or serious burns and if condition persists for more than 4 days or worsens.

Keep out of reach of children. If swallowed, get medical help and contact a Poison Control Center right away.

DOSAGE AND ADMINISTRATION

Directions •read all package directions and warnings before use. When using this product use only as directed. Apply a thin layer to affected area and massage gently as soon as possible after minor injury. Apply 3X a day or as needed •Sensitivity Test for a New User. Apply sparingly to one or two small affected areas during the first 3 days. •if no discomfort occurs, follow the direction stated above.

Other information • do not use if glued carton end flaps are open or if the tube seal is broken. •store at room temperature.

Inactive ingredients:

Aloe Barbadensis Leaf Juice†

Avena Sativa (Oat) Kernel Flour

Beeswax

Butyrospermum Parkii (Shea) Butter

Calendula Officinalis Flower Extract

Cetearyl Alcohol

Cetyl Alcohol

Dimethicone

Ethylhexylglycerin

Helianthus Annuus (Sunflower) Seed Oil

Isopropyl Palmitate

Olea Europaea (Olive) Fruit Oil

Panthenol

Phenoxyethanol

Polysorbate 60

Sodium Hydroxide

Sodium PCA

Sodium Phytate

Tocopheryl Acetate

Water (Aqua)

Zinc PCA

†Certified Organic Ingredient — Mayacert Certifier

QUESTIONS

Questions? 1-800-279-7282 M-F 8am-4pm PST

Speed healing of wounds, sores, cuts, scrapes, chafing & minor burns
AP4 BOTANICAL
ALOE VERA COMPLEX
Calendula
Homeopathic Medicine

- Uses have not been evaluated by Food and Drug Administration.

-X is homeopathic dilutions.

www.triderma.com

Mfd. by: Genuine Virgin Aloe corp., Anaheim, CA 92807 Made in USA

EXPERTS IN SKIN HEALING SINCE 1992

Pressure Sore Relief is specifically formulated to help protect and promote relief for red, irritated, chapped or cracked skin. Use daily to help protect against skin breakdown.

This non-greasy formula has become a customer favorite for those that use a wheelchair, have prosthetic limbs, or are bed-ridden to help keep skin healthy.